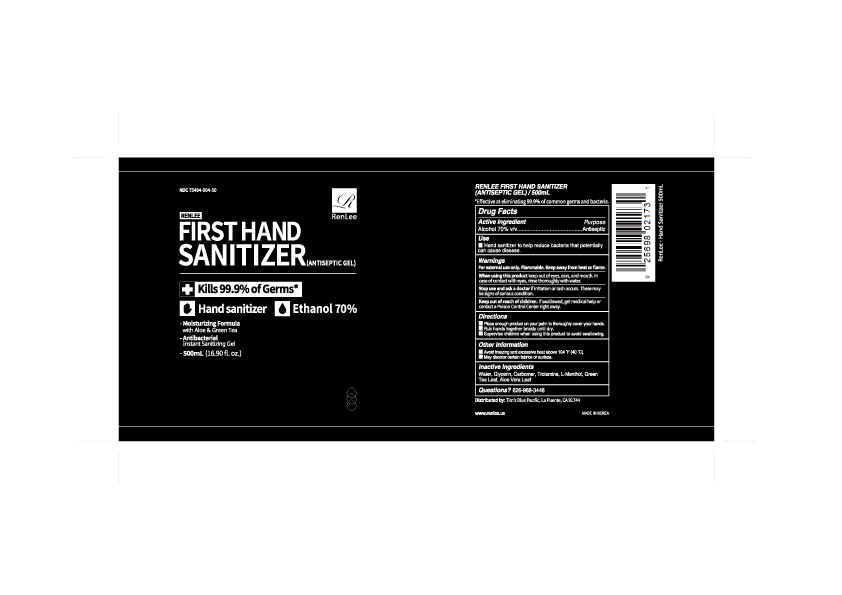 DRUG LABEL: RENLEE FIRST HAND SANITIZER
NDC: 75484-004 | Form: GEL
Manufacturer: SYNERGYPLANETS INC.
Category: otc | Type: HUMAN OTC DRUG LABEL
Date: 20200622

ACTIVE INGREDIENTS: ALCOHOL 70 mL/100 mL
INACTIVE INGREDIENTS: TROLAMINE; LEVOMENTHOL; GREEN TEA LEAF; ALOE VERA LEAF; CARBOMER HOMOPOLYMER TYPE B (ALLYL PENTAERYTHRITOL CROSSLINKED); WATER; GLYCERIN

Active Ingredient

Alcohol 70% v/v

Purpose

Antiseptic

Use

- Hand sanitizer to help reduce bacteria that potentially can cause disease.

Warnings

For external use only. Flammable. Keep away from heat or flame.

When using this product keep out of eyes, ears, and mouth. In case of contact with eyes, rinse thoroughly with water.

Stop use and ask a doctor if irritation or rash occurs. These may be signs of serious condition.

Keep out of reach of children. If swallowed, get medical help or contact a Poison Control Center right away.

Directions

- Place enough product on your palm to thoroughly cover your hands.
- Rub hands together briskly until dry.
- Supervise children when using this product to avoid swallowing.

Other Information

- Avoid freezing and excessive heat above 104°F(40°C).
- May discolor certain fabrics or surface.

Inactive Ingredients

Water, Glycerin, Carbomer, Trolamine, L-Menthol, Green Tea Leaf, Aloe Vera Leaf

Qusetions?

626-968-3448